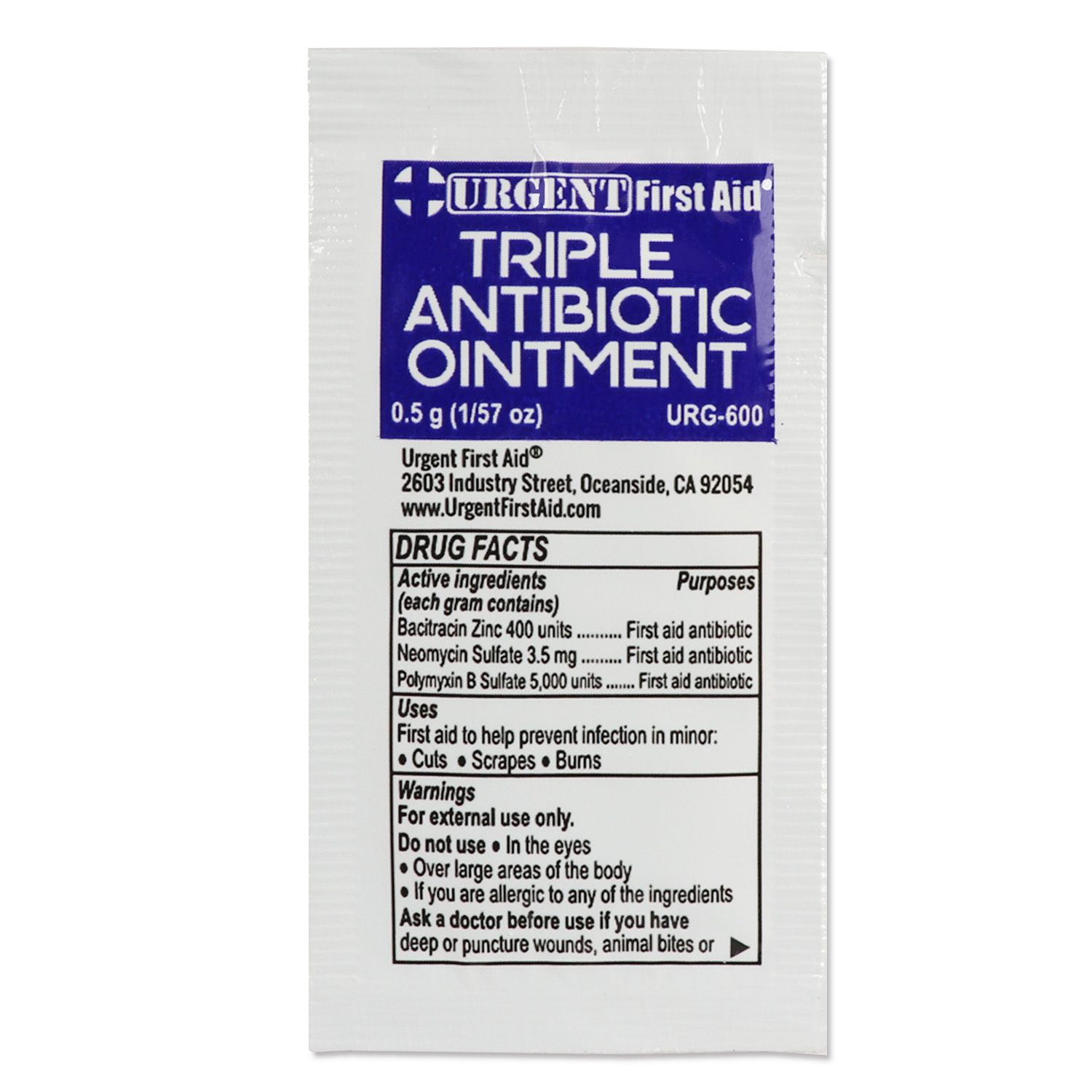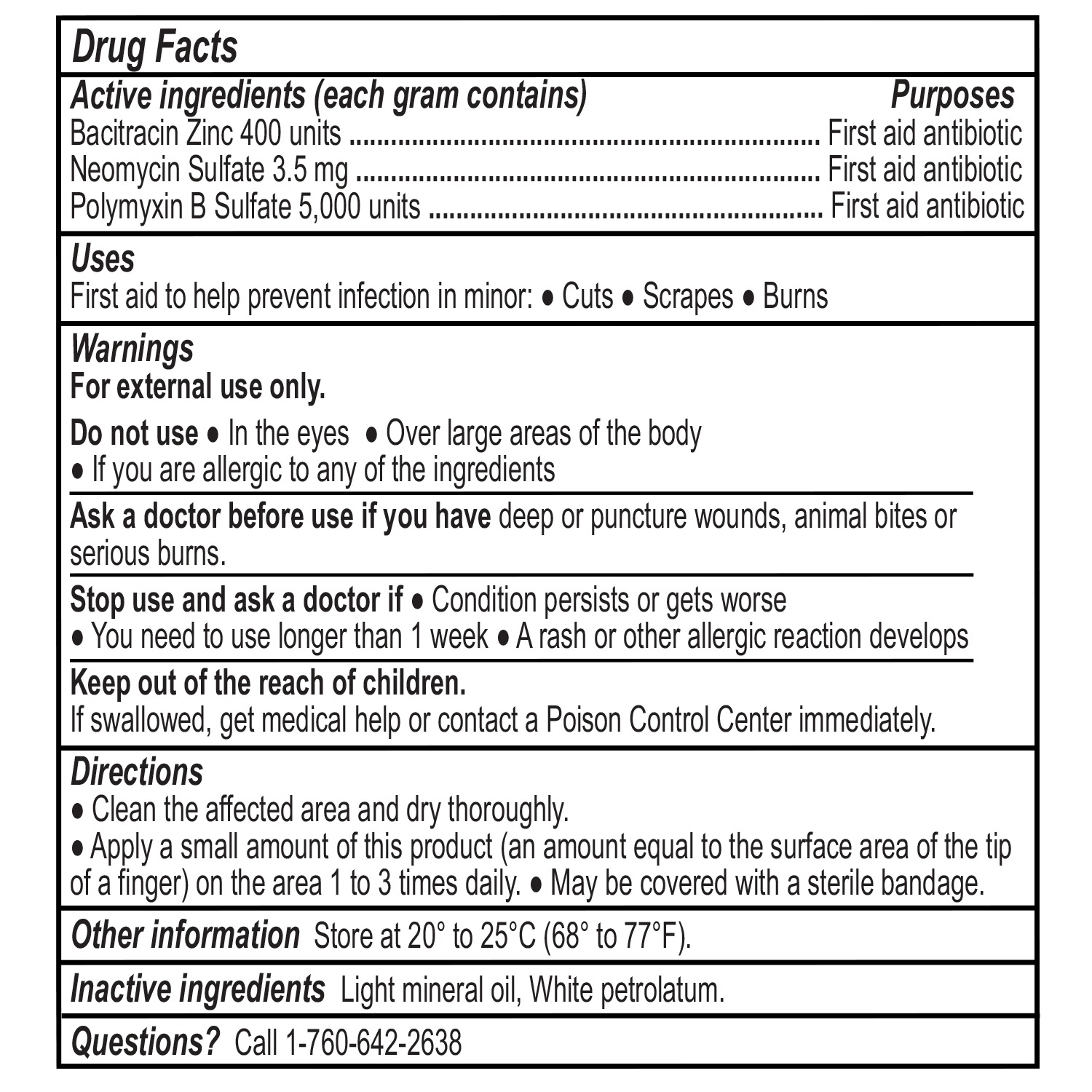 DRUG LABEL: Triple Antibiotic
NDC: 73233-125 | Form: OINTMENT
Manufacturer: Express Companies, Inc.
Category: otc | Type: HUMAN OTC DRUG LABEL
Date: 20250527

ACTIVE INGREDIENTS: BACITRACIN ZINC 400 [iU]/1 g; POLYMYXIN B SULFATE 5000 [iU]/1 g; NEOMYCIN SULFATE 5 mg/1 g
INACTIVE INGREDIENTS: LIGHT MINERAL OIL; WHITE PETROLATUM

Active Ingredients

Bacitracin Zinc 400 Units

Neomycin Sulfate 3.5mg

Polymyxin B Sulfate 5,000 Units

Uses

First aid to help prevent infection in minor:

- Cuts
- Scrapes
- Burns

Inactive Ingredients

Light Mineral Oil, White petrolatum

Warnings

For external use only.

Do Not Use:

- In the eyes
- Over large areas of the body
- If you are allergic to any of the ingredients

Ask a doctor before use if you have:

- Deep or Puncture Wounds
- Animal Bites
- Serious Burns

Stop use and ask a doctor before use if:

- Condition persists or gets worse
- You need to use longer than 1 week
- A rash or other allergic reaction develops

Questions?

Call 1-760-642-2638

Other Information

Store at 68° to 77°F (20° to 25°C)

Directions

- Clean the affected area and dry thoroughly
- Apply a small amount of this product (an amount equal to the surface area of the tip of a finger) on the area 1 to 3 times daily
- May be covered with a sterile bandageDirections

Keep out of reach of childern

If swallowed, get medical help or contact a Posison Control Center immediately.

Purpose

Triple Antibiotic Ointment to treat minor cuts, scrapes, and burns.